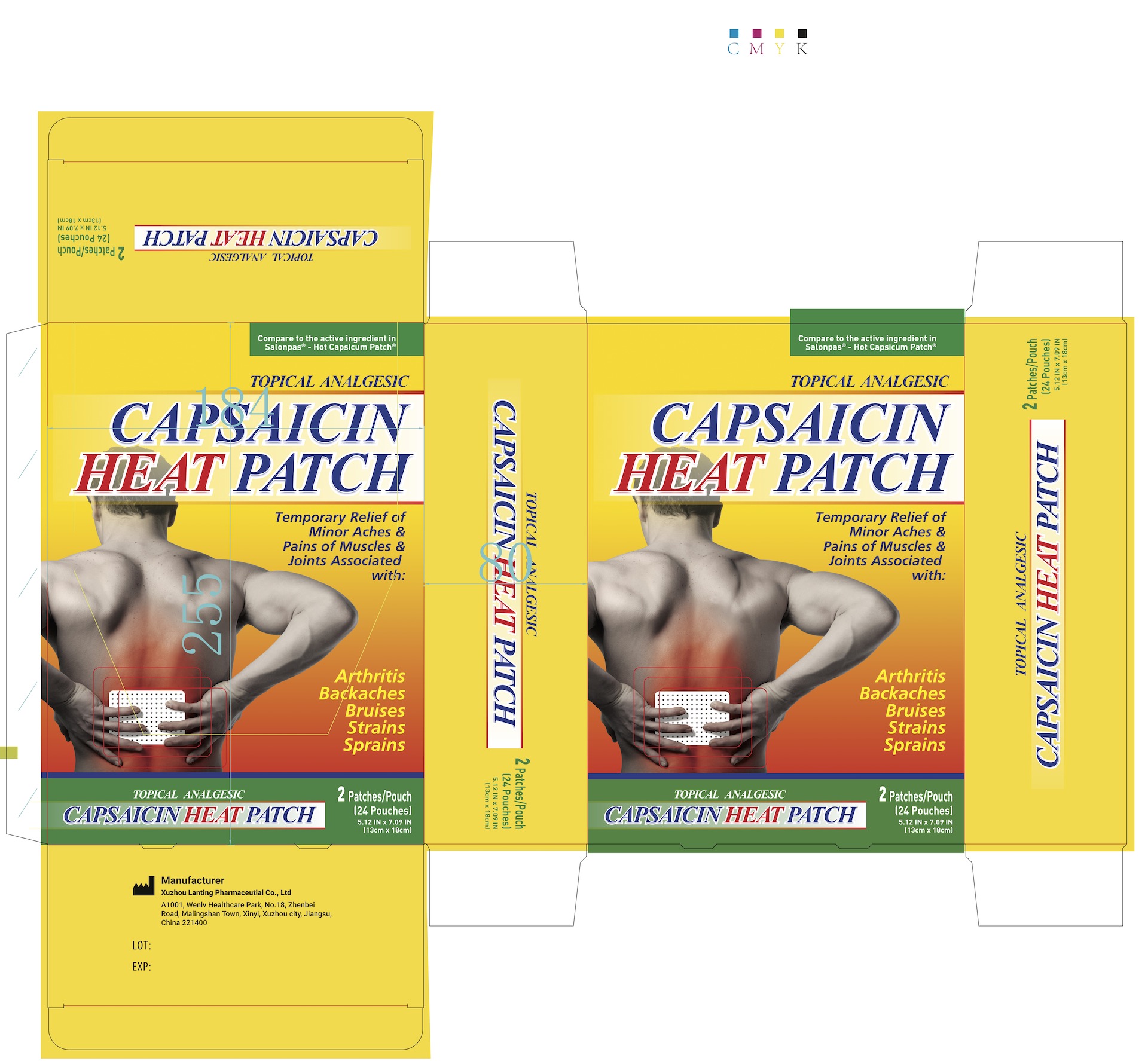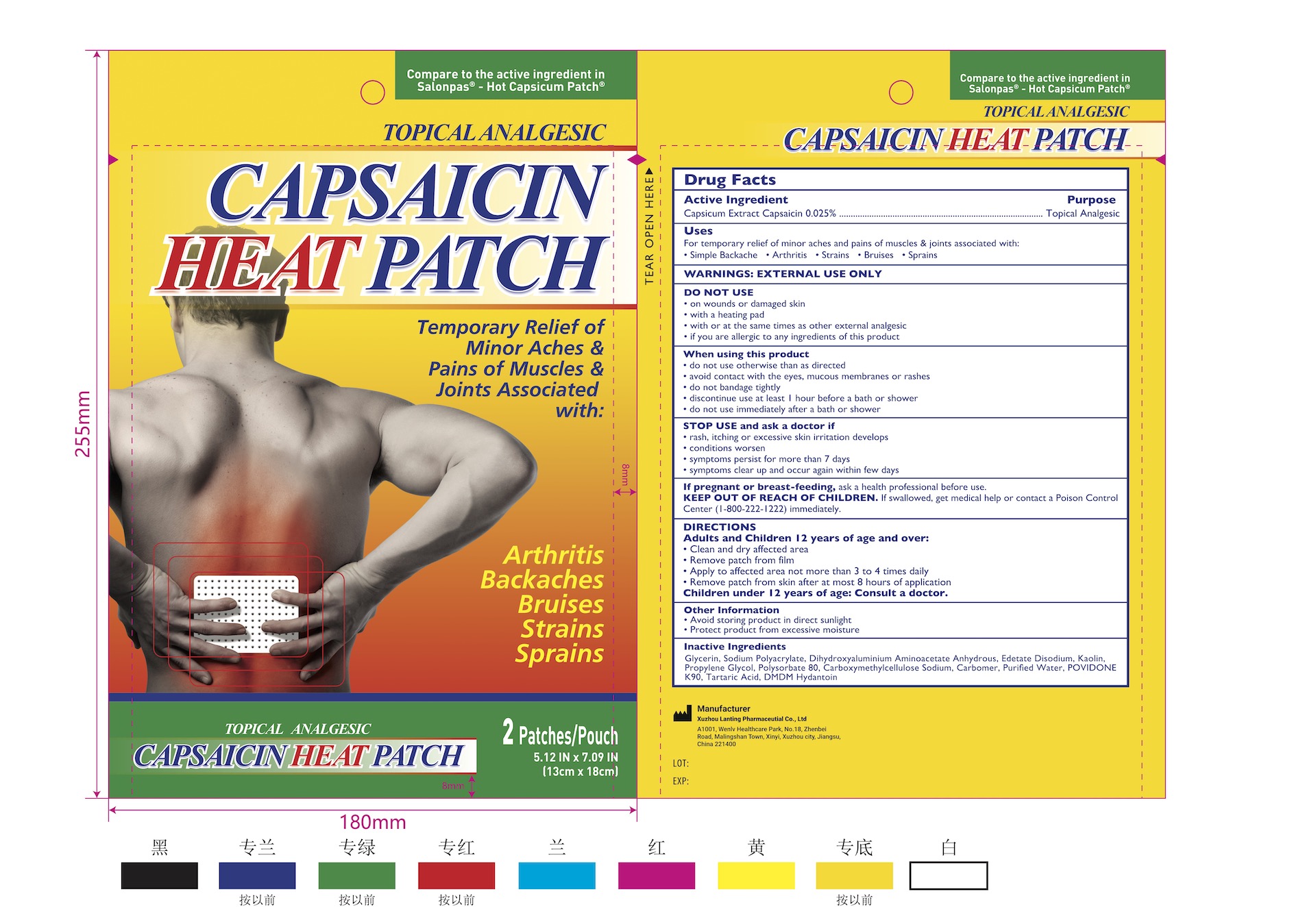 DRUG LABEL: 0.025% Capsaicin Pain relief Patch
NDC: 85323-005 | Form: PATCH
Manufacturer: Xuzhou Lanting Pharmaceutical Co., Ltd
Category: otc | Type: HUMAN OTC DRUG LABEL
Date: 20250610

ACTIVE INGREDIENTS: CAPSAICIN 0.025 g/100 g
INACTIVE INGREDIENTS: KAOLIN; CARBOMER 934; EDETATE DISODIUM; PROPYLENE GLYCOL; POLYSORBATE 80; SODIUM POLYACRYLATE (2500000 MW); GLYCERIN; DMDM HYDANTOIN; DIHYDROXYALUMINUM AMINOACETATE ANHYDROUS; WATER; TARTARIC ACID; POVIDONE K90; CARBOXYMETHYLCELLULOSE SODIUM

85323-005, 0.025% Capsaicin Pain relief Patch

0.025% Capsaicin Pain relief Patch, Package NDC Code: 85323-005-01

Active Ingredient

Active Ingredient: 0.025% Capsaicin

Purpose

Purpose: Topical anesthetic

Warnings

Warnings: For external use only

Do not use

- on wounds or damaged skin
- with a heating pad
- with or at the same times as other external analgesic
- if you are allergic to any ingredients of this product

When using this product

- do not use otherwise than as directed
- avoid contact with the eyes, mucous membranes or rashes
- do not bandage tightly
- discontinue use at least 1 hour before a bath or shower
- do not use immediately after a bath or shower

Stop use and ask a doctor if

- rash, itching or excessive skin irritation develops
- condition worsen
- symptoms persist for more than 7 days
- symptoms clear up and occur again within few days

If pregnant or breast-feeding, ask a health professional before use.

Keep out of reach of children. If swallowed, get medical help or contact a Poison Control Center (1-800-222-1222) immediately.

Uses

For temporary relief of minor aches and pains of muscles & joints associated with:

- Simple Backache
- Arthritis
- Strains
- Bruises
- Sprains

Other information

- Avoid storing product in direct sunlight
- Protect product from excessive moisture

Inactive Ingredients

Glycerin, Sodium Polyacrylate, Dihydroxyaluminum Aminoacetate Anhydrous, Edetate Disodium, Kaolin, Propylene Glycol, Polysorbate 80, Carboxymethylcellulose Sodium, Carbomer, Purified Water, POVIDONE K90, Tartaric Acid, Dmdm Hydantoin.

Keep out of reach of children. If swallowed, get medical help or contact a Poison Control Center (1-800-222-1222) immediately.

INDICATIONS AND USAGE

For temporary relief of minor aches and pains of muscles & joints associated with:

- Simple Backache
- Arthritis
- Strains
- Bruises
- Sprains

Adult and children 12 years of age and over:

- Clean and dry affected area
- Remove patch from film
- Apply to affected area not more than 3 to 4 times daily
- Remove patch from skin after at most 8 hours of application

Children under 12 years of age: consult a doctor.

Directions

Adult and children 12 years of age and over:

- Clean and dry affected area
- Remove patch from film
- Apply to affected area not more than 3 to 4 times daily
- Remove patch from skin after at most 8 hours of application

Children under 12 years of age: consult a doctor.